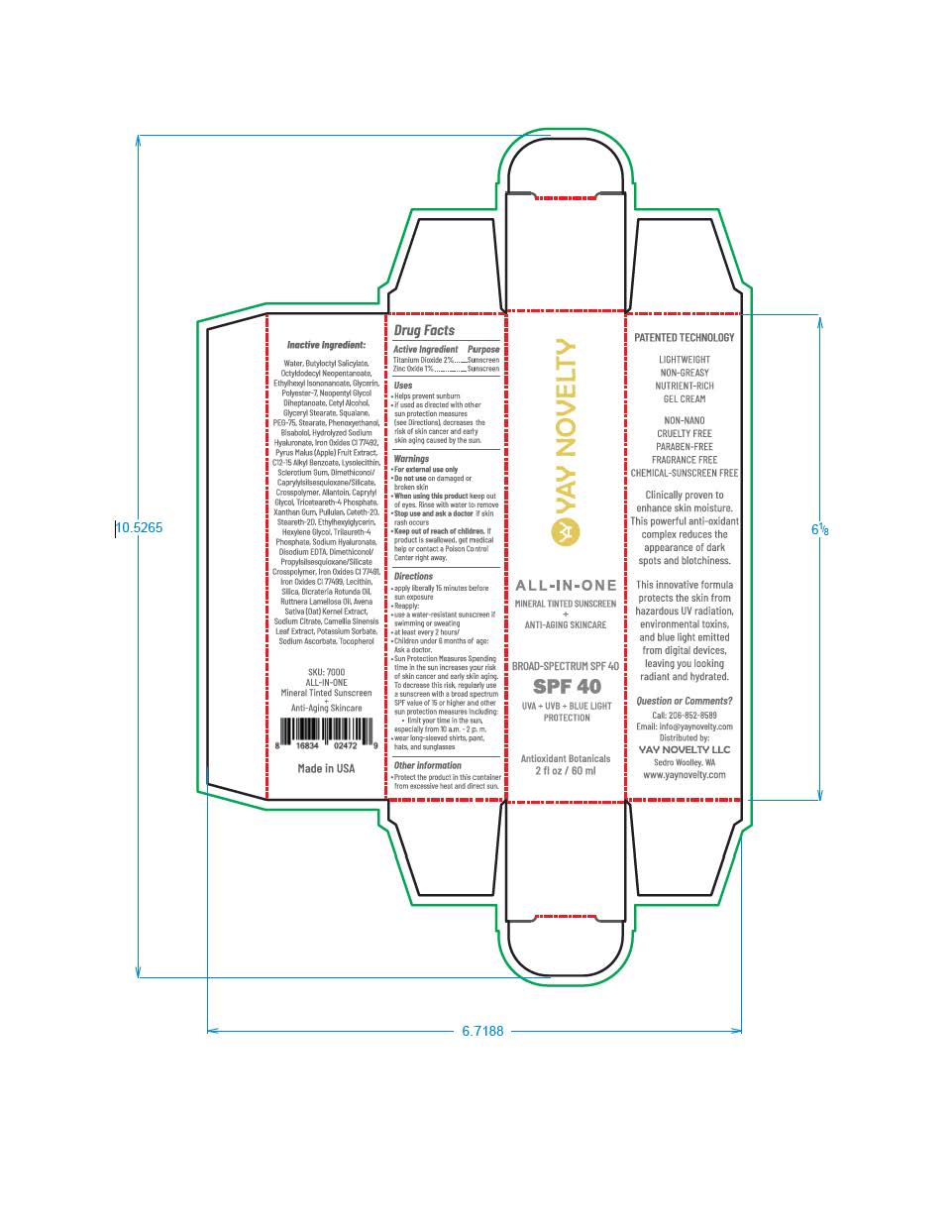 DRUG LABEL: YAY NOVELTY ALL-IN-ONE
NDC: 83336-0391 | Form: LOTION
Manufacturer: YAY Novelty
Category: otc | Type: HUMAN OTC DRUG LABEL
Date: 20251114

ACTIVE INGREDIENTS: ZINC OXIDE 9.7 mg/1 mL; TITANIUM DIOXIDE 19.4 mg/1 mL
INACTIVE INGREDIENTS: FERROSOFERRIC OXIDE; BUTYLOCTYL SALICYLATE; POLYESTER-7; GLYCERIN; NEOPENTYL GLYCOL DIHEPTANOATE; GLYCERYL STEARATE SE; ALKYL (C12-15) BENZOATE; FERRIC OXIDE RED; ALLANTOIN; CAPRYLYL GLYCOL; AVENA SATIVA WHOLE; DICRATERIA ROTUNDA OIL; DISODIUM EDTA-COPPER; CAMELLIA SINENSIS WHOLE; TRICETEARETH-4 PHOSPHATE; PULLULAN; XANTHAN GUM; STEARETH-20; HEXYLENE GLYCOL; TRILAURETH-4 PHOSPHATE; SODIUM ASCORBATE; OCTYLDODECYL NEOPENTANOATE; CETYL ALCOHOL; SQUALANE; PEG-75 STEARATE; PHENOXYETHANOL; .ALPHA.-BISABOLOL, (+)-; ETHYLHEXYLGLYCERIN; DIMETHICONOL/PROPYLSILSESQUIOXANE/SILICATE CROSSPOLYMER (450000000 MW); LECITHIN, SOYBEAN; SILICON DIOXIDE; ETHYLHEXYL ISONONANOATE; CETETH-20; POTASSIUM SORBATE; TOCOPHEROL; RUTTNERA LAMELLOSA OIL; FERRIC OXIDE YELLOW

YAY NOVELTY ALL-IN-ONE